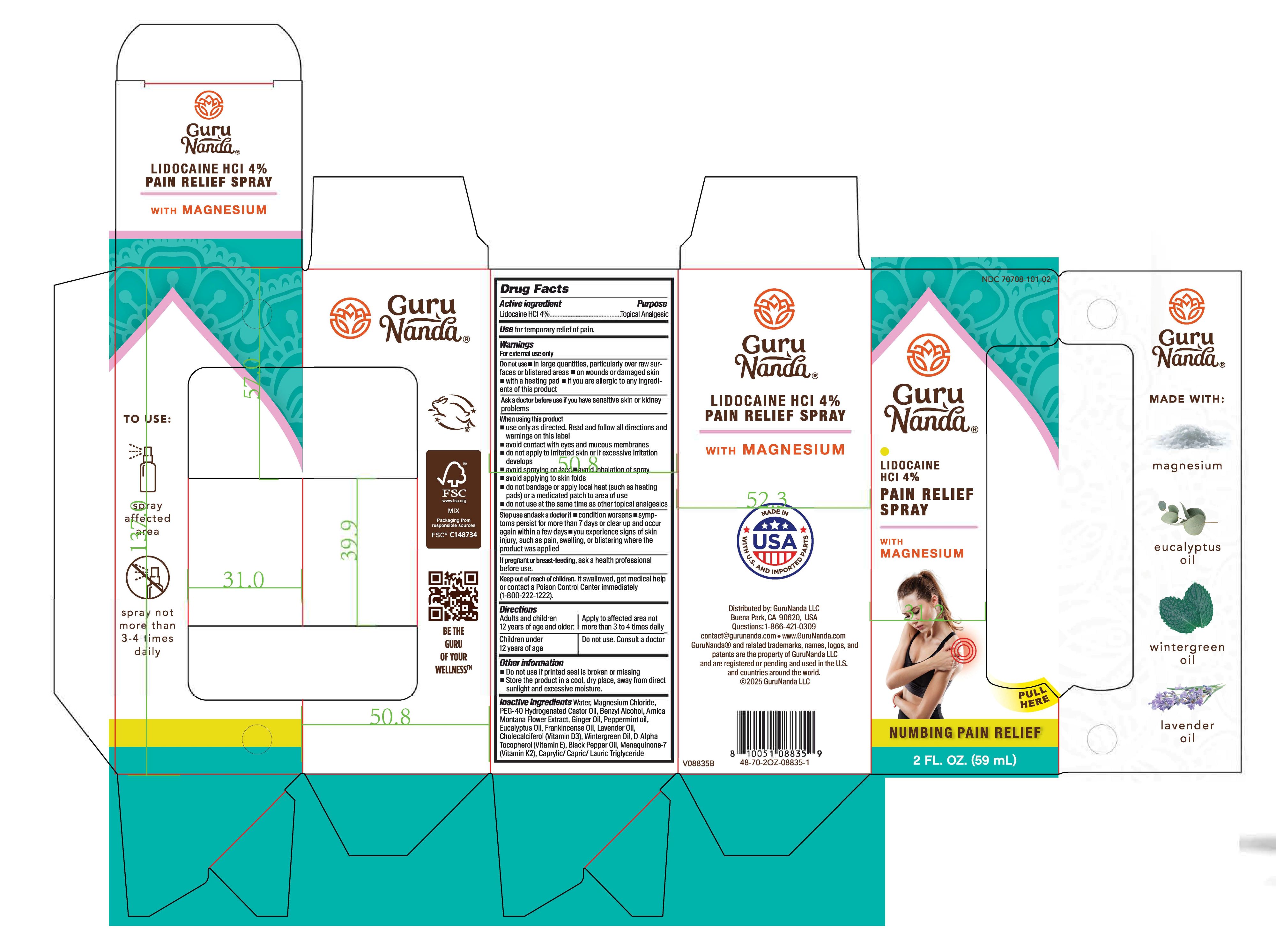 DRUG LABEL: GuruNanda Pain Relief
NDC: 70708-101 | Form: SPRAY
Manufacturer: GuruNanda, LLC.
Category: otc | Type: HUMAN OTC DRUG LABEL
Date: 20251110

ACTIVE INGREDIENTS: LIDOCAINE HYDROCHLORIDE 40 mg/1 mL
INACTIVE INGREDIENTS: METHYL SALICYLATE; .ALPHA.-TOCOPHEROL, D-; CAPRYLIC/CAPRIC/LAURIC TRIGLYCERIDE; GINGER OIL; BLACK PEPPER OIL; MAGNESIUM CHLORIDE; PEPPERMINT OIL; WATER; BENZYL ALCOHOL; ARNICA MONTANA FLOWER; CHOLECALCIFEROL; PEG-40 HYDROGENATED CASTOR OIL; LAVENDER OIL; MENAQUINONE 7; FRANKINCENSE OIL; EUCALYPTUS OIL

GuruNanda Lidocaine 4% Rain Relief Spray with Mangnesium

ACTIVE INGREDIENT

Lidocaine HCI 4%

PURPOSE

Topical Analgesic

Uses

for temporary relief of pain

Warnings

For external use only

Do not use

- in large quantities, particularly over raw surfaces or blistered areas
- on wounds or damaged skin
- with a heating pad
- if you are allergic to any ingredients of this product

Ask a doctor before use if you have

sensitive skin or kidney problems

When using this product

- use only as directed. Read and follow all directions and warnings on this label
- avoid contact with eyes and mucous membranes
- do not apply to irritated skin or if excessive irriation develops
- avoid spraying on face
- avoid inhalation of spray
- avoid applying to skin folds
- do not bandage or apply local heat (such as heating pads) or a medicated patch to area of use
- do not use at the same time as other topical analgesic

Stop use and ask a doctor if

- condition worsens
- symptoms persist for more than 7 days or clear up and occur again within a few days
- you experience signs of skin injury, such as pain, swelling, or blistering where the product was applied

If pregnant or breast-feeding,

ask a health professional before use.

Keep out of reach of children

If swallowed, get medical help or contact a Poison Control Center immediately (1-800-222-1222)

Directions

Adults and children 12 years of age and older: apply to affected area not more than 3 to 4 times daily

Children under 12 years of age: Do not use. Consult a doctor

Other information

- Do not use if printed seal is broken or missing
- Store the product in a cool, dry place, away from direct sunlight and excessive moisture

Inactive ingredients

Water, Magnesium Chloride, PEG-40 Hydrogenated Castor Oil, Benzyl Alcohol, Arnica Montana Flower Extract, Ginger Oil, Peppermint Oil, Cholecalciferol (Vitamin D3), Wintergreen Oil, D-Alpha Tocopherol (Vitamin E), Black Pepper Oil, Menaquinone-7 (Vitamin K2), Caprylic/Capric/Lauric Triglyceride